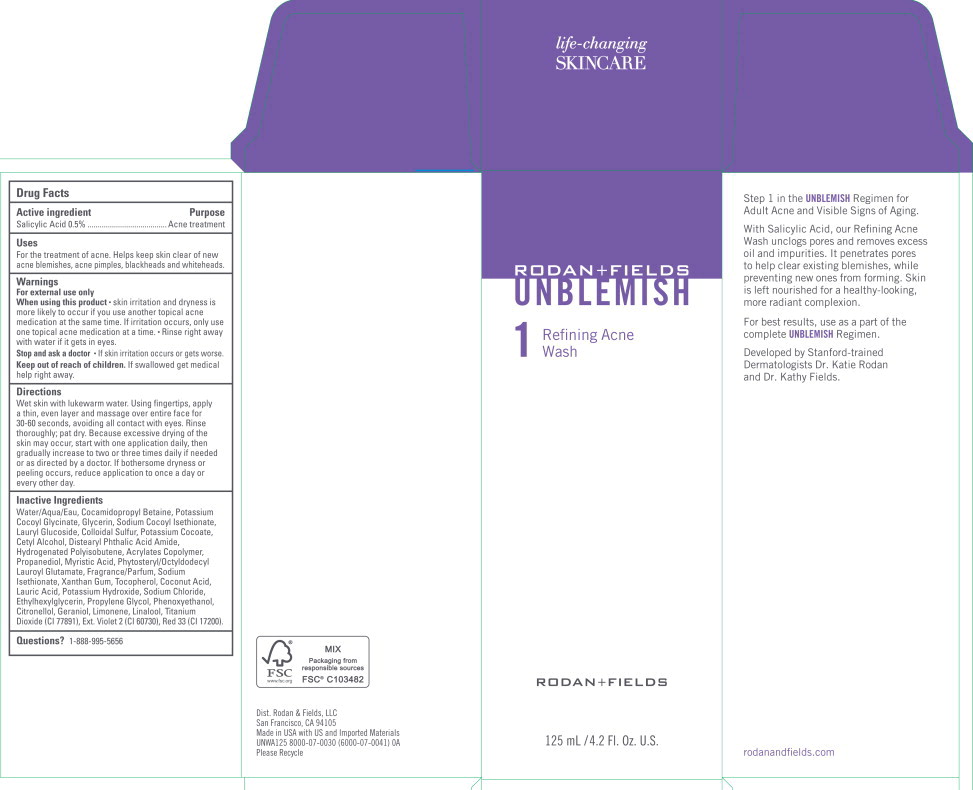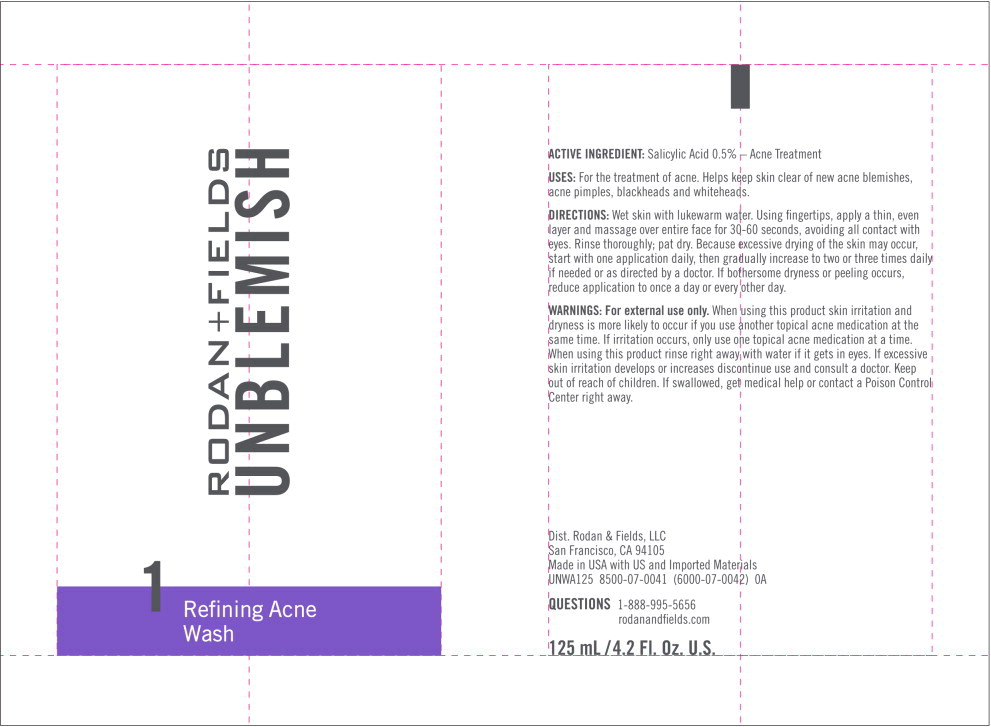 DRUG LABEL: UNBLEMISH Refining Acne Wash
NDC: 14222-2111 | Form: CREAM
Manufacturer: Rodan & Fields
Category: otc | Type: HUMAN OTC DRUG LABEL
Date: 20231213

ACTIVE INGREDIENTS: SALICYLIC ACID 0.005 g/1 mL
INACTIVE INGREDIENTS: BUTYL ACRYLATE/METHYL METHACRYLATE/METHACRYLIC ACID COPOLYMER (18000 MW); CETYL ALCOHOL; COCAMIDOPROPYL BETAINE; COCONUT ACID; DISTEARYL PHTHALAMIC ACID; ETHYLHEXYLGLYCERIN; GLYCERIN; HYDROGENATED POLYBUTENE (1300 MW); LAURIC ACID; LAURYL GLUCOSIDE; MYRISTIC ACID; PHENOXYETHANOL; PHYTOSTERYL/OCTYLDODECYL LAUROYL GLUTAMATE; POTASSIUM COCOATE; POTASSIUM COCOYL GLYCINATE; POTASSIUM HYDROXIDE; PROPANEDIOL; PROPYLENE GLYCOL; D&C RED NO. 33; SODIUM CHLORIDE; SODIUM COCOYL ISETHIONATE; SODIUM ISETHIONATE; SULFUR; TITANIUM DIOXIDE; TOCOPHEROL; D&C VIOLET NO. 2; WATER; XANTHAN GUM

Drug Facts

Active ingredient

Salicylic Acid 0.5%

Purpose

Acne treatment

Uses

For the treatment of acne. Helps keep skin clear of new acne blemishes, acne pimples, blackheads and whiteheads.

Warnings

For external use only

When using this product

- skin irritation and dryness is more likely to occur if you use another topical acne medication at the same time. If irritation occurs, only use one topical acne medication at a time.
- Rinse right away with water if it gets in eyes.

Stop and ask a doctor

- If skin irritation occurs or gets worse.

Keep out of reach of children. If swallowed get medical help right away.

Directions

Wet skin with lukewarm water. Using fingertips, apply a thin, even layer and massage over entire face for 30-60 seconds, avoiding all contact with eyes. Rinse thoroughly; pat dry. Because excessive drying of the skin may occur, start with one application daily, then gradually increase to two or three times daily if needed or as directed by a doctor. If bothersome dryness or peeling occurs, reduce application to once a day or every other day.

Inactive Ingredients

Water/Aqua/Eau, Cocamidopropyl Betaine, Potassium Cocoyl Glycinate, Glycerin, Sodium Cocoyl lsethionate, Lauryl Glucoside, Colloidal Sulfur, Potassium Cocoate, Cetyl Alcohol, Distearyl Phthalic Acid Amide, Hydrogenated Polyisobutene, Acrylates Copolymer, Propanediol, Myristic Acid, Phytosteryl/Octyldodecyl Lauroyl Glutamate, Fragrance/Parfum, Sodium lsethionate, Xanthan Gum, Tocopherol, Coconut Acid, Lauric Acid, Potassium Hydroxide, Sodium Chloride, Ethylhexylglycerin, Propylene Glycol, Phenoxyethanol, Citronellol, Geraniol, Limonene, Linalool, Titanium Dioxide (Cl 77891), Ext. Violet 2 (Cl 60730), Red 33 (Cl 17200).

Questions?

1-888-995-5656

Principal Display Panel – 125 mL Carton Label

RODAN+FIELDS
UNBLEMISH

1
Refining Acne
Wash

RODAN+FIELDS

125 mL/4.2 Fl. Oz. U.S.

Principal Display Panel – 125 mL Tube Label

RODAN+FIELDS
UNBLEMISH

1
Refining Acne
Wash